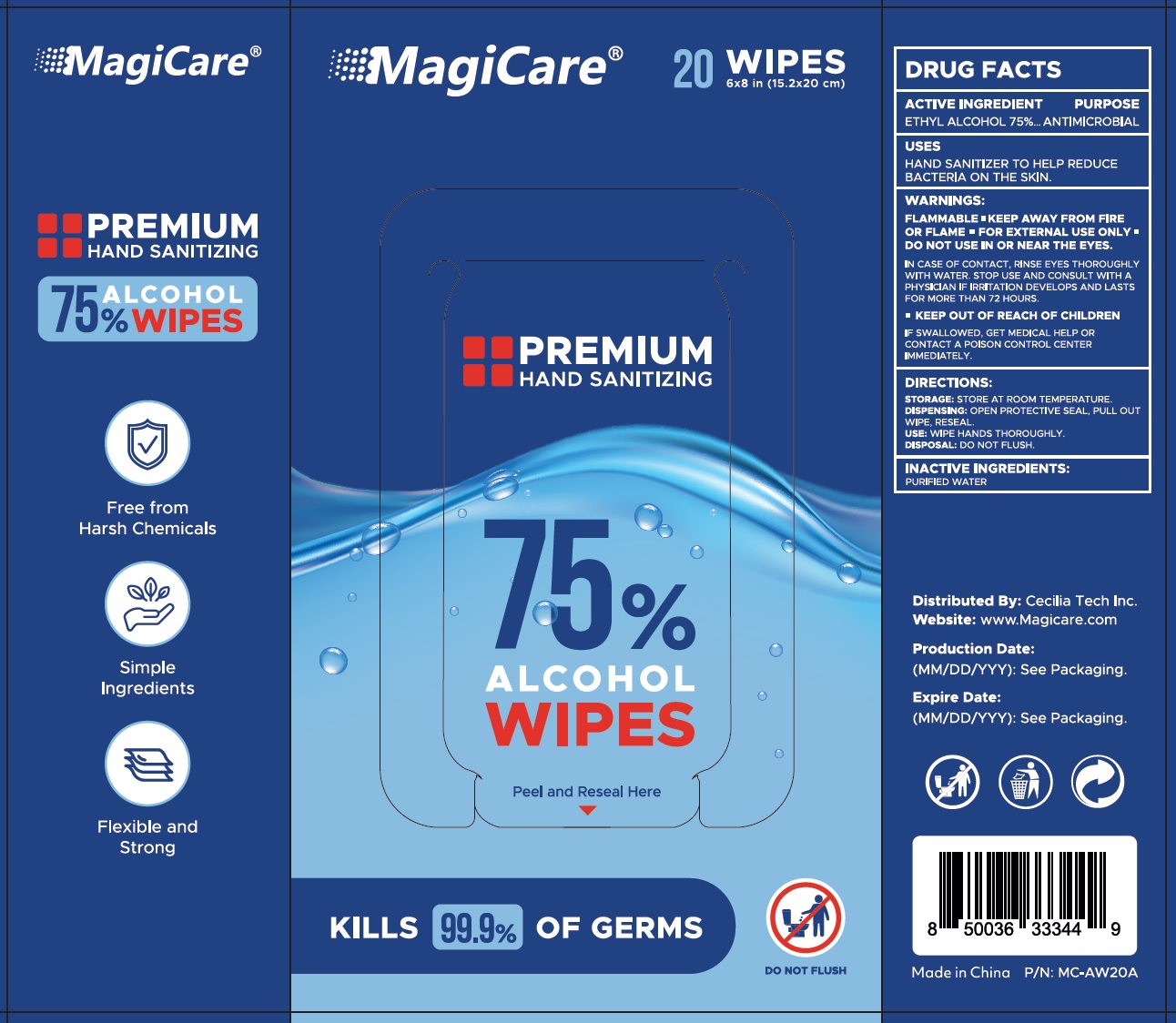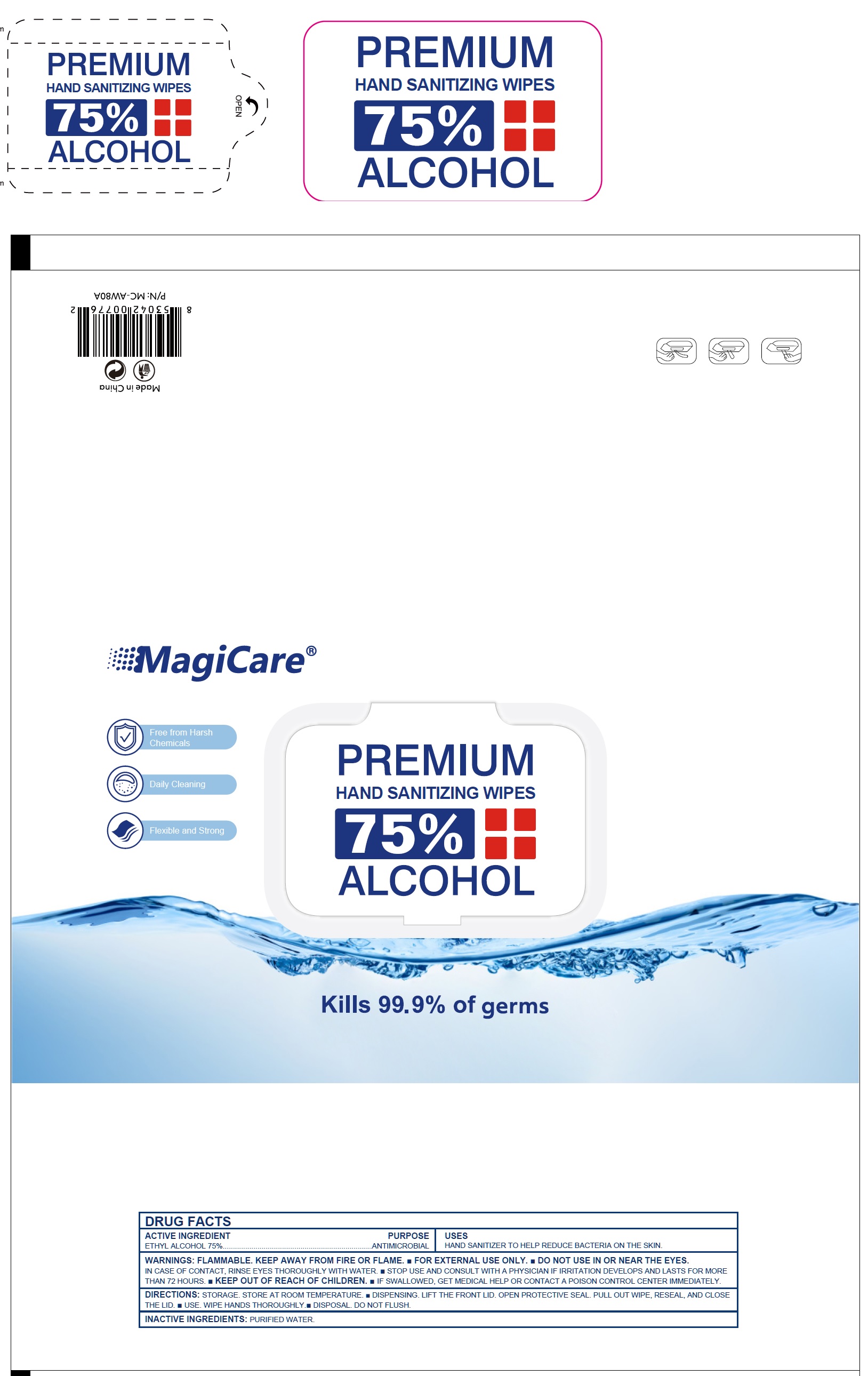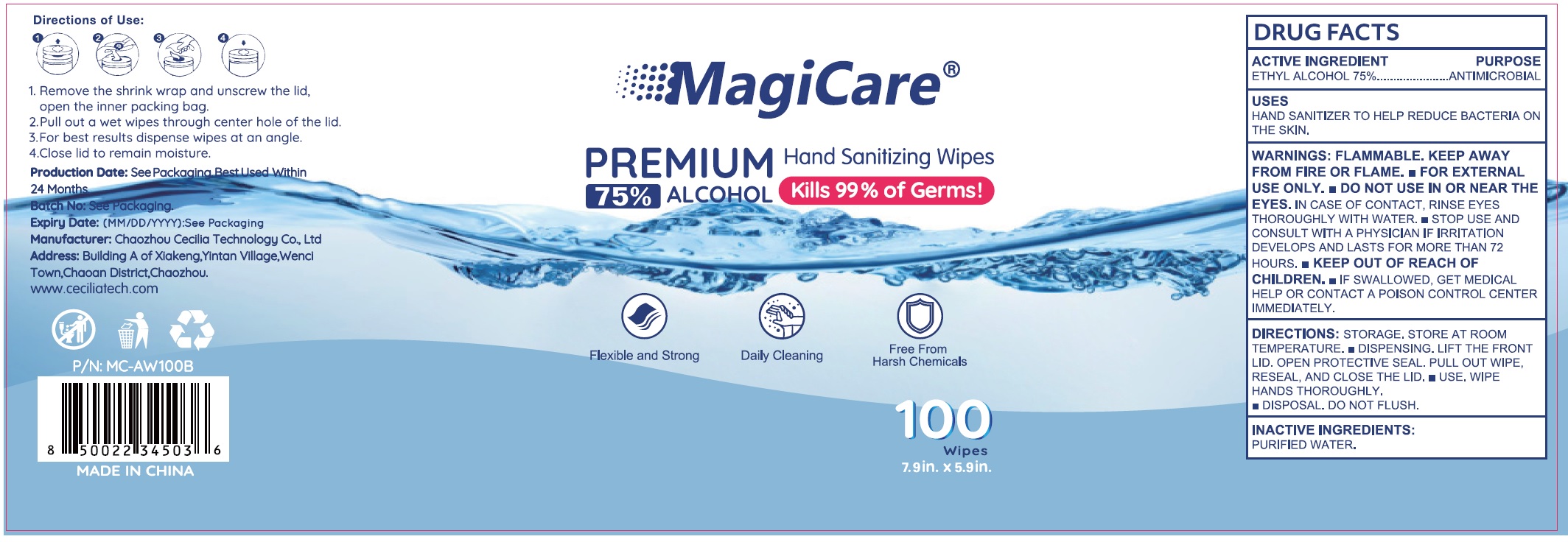 DRUG LABEL: MagiCare Premium Hand Sanitizing Wipes
NDC: 85276-104 | Form: CLOTH
Manufacturer: Cecilia Tech Inc.
Category: otc | Type: HUMAN OTC DRUG LABEL
Date: 20250923

ACTIVE INGREDIENTS: ALCOHOL 75 mL/100 mL
INACTIVE INGREDIENTS: WATER

MagiCare Premium Hand Sanitizing Wipes

ACTIVE INGREDIENT

ETHYL ALCOHOL 75%

PURPOSE

ANTIMICROBIAL

USES

HAND SANITIZER TO HELP REDUCE BACTERIA ON THE SKIN.

WARNINGS:

FLAMMABLE. KEEP AWAY FROM FIRE OR FLAME. • FOR EXTERNAL USE ONLY.

DO NOT USE

- IN OR NEAR THE EYES. IN CASE OF CONTACT, RINSE EYES THOROUGHLY WITH WATER.

STOP USE AND CONSULT WITH A PHYSICIAN

IF IRRITATION DEVELOPS AND LASTS FOR MORE THAN 72 HOURS.

KEEP OUT OF REACH OF CHILDREN.

- IF SWALLOWED, GET MEDICAL HELP OR CONTACT A POISON CONTROL CENTER IMMEDIATELY.

DIRECTIONS:

STORAGE: STORE AT ROOM TEMPERATURE.

- DISPENSING: LIFT THE FRONT LID. OPEN PROTECTIVE SEAL. PULL OUT WIPE, RESEAL, AND CLOSETHE LID.
- USE: WIPE HANDS THOROUGHLY.
- DISPOSAL: DO NOT FLUSH.

INACTIVE INGREDIENTS:

PURIFIED WATER